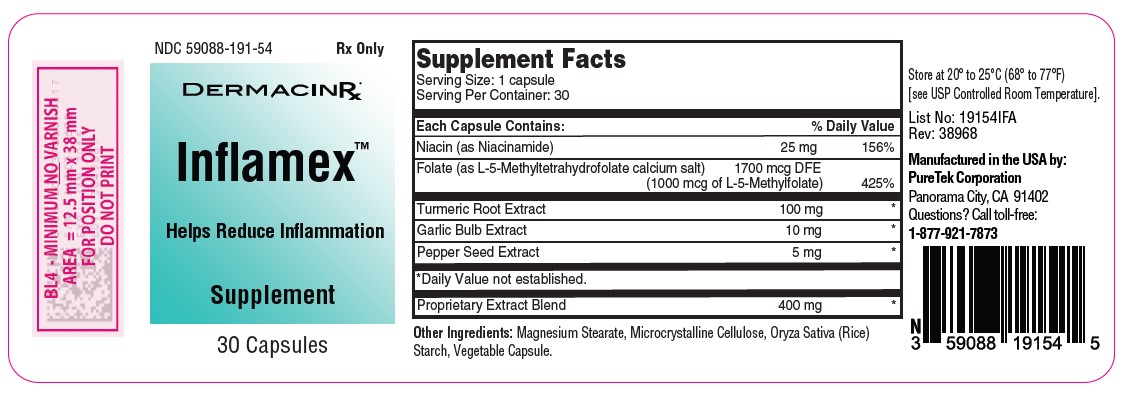 DRUG LABEL: Inflamex
NDC: 59088-191 | Form: CAPSULE
Manufacturer: PureTek Corporation
Category: prescription | Type: HUMAN PRESCRIPTION DRUG LABEL
Date: 20240612

ACTIVE INGREDIENTS: BLACK PEPPER 5 mg/1 1; NIACINAMIDE 25 mg/1 1; GARLIC 10 mg/1 1; TURMERIC 100 mg/1 1; LEVOMEFOLATE CALCIUM 1700 ug/1 1
INACTIVE INGREDIENTS: MICROCRYSTALLINE CELLULOSE; MAGNESIUM STEARATE; GELLAN GUM (LOW ACYL); STARCH, RICE; HYPROMELLOSES

Inflamex

DESCRIPTION:

lnflamex™ is a unique formulation of selected natural ingredients such as Turmeric, Black Pepper, Garlic and Proprietary Extract Blend combined with Niacin and Folate. This potent blend is designed to support your body's response to inflammation and its natural healing processes.

Each capsule contains:

Niacin (as Niacinamide) ....……………………………….…......25 mg
Folate (as L-5-Methyltetrahydrofolate calcium salt) ..........1700 mcg DFE
(1000 mcg of L-5-Methylfolate)
Turmeric Root Extract……………………………….…………100 mg
Garlic Bulb Extract……………………………….…………….. 10 mg
Pepper Seed Extract……………………………….…………….. 5 mg

Proprietary Extract Blend ………………………….…………. 400 mg

Other Ingredients:

Magnesium Stearate, Microcrystalline Cellulose, Oryza Sativa (Rice) Starch, Vegetable Capsule.

Contraindications:

This product is contraindicated in patients with a known hypersensitivity to any of the ingredients. lnflamex™ is contraindicated in patients with gastrointestinal conditions, such as gastric ulcers or gastroesophageal reflux disease (GERD), as they may experience irritation or worsening of symptoms due to the presence of ingredients like garlic and black pepper. Patients with blood clotting disorders or who are on anticoagulant therapy should use caution when consuming high doses of ingredients like garlic, turmeric, and black pepper, as they may have mild blood-thinning effects.

Warnings:

Tell your doctor if you have: kidney problems, thyroid disease. This medication should be used as directed during pregnancy or while breast-feeding. Consult your doctor. Administration of folate alone is improper therapy for pernicious anemia and other megaloblastic anemias in which vitamin B12 is deficient.

Precautions:

Folate in doses above 0.1 mg daily may obscure pernicious anemia, in that hematologic remission can occur while neurological manifestations remain progressive. There is a potential danger in administering folate to patients with undiagnosed anemia since folate may obscure the diagnosis of pernicious anemia by alleviating the hematologic manifestations of the disease while allowing the neurologic complications to progress. This may result in severe nervous system damage before the correct diagnosis is made. The patient's medical conditions and consumption of other drugs, herbs, and/or supplements should be considered.

Pregnancy and Lactation:

Not recommended for use during pregnancy or lactation without consulting with a healthcare professional.

For use on the order of a licensed healthcare practitioner.
If a patient experiences any side effects, call your doctor. To report side effects, call PureTek Corporation at 1-877-921-7873 or FDA at 1-800-FDA-1088 or www.fda.gov/medwatch.

Adverse Reactions:

Allergic reactions to any of the ingredients can occur, ranging from mild skin irritation to severe anaphylaxis in rare cases. Allergic sensitization has been reported following both oral and parenteral administration of folate.

Niacinamide, a form of niacin, may cause flushing, itching, and tingling sensations in some individuals, particularly when taken in higher doses. This effect is usually harmless but can be uncomfortable. Some individuals may experience gastrointestinal symptoms such as nausea, bloating, or diarrhea, especially when consuming higher doses of certain ingredients like garlic and black pepper. Certain ingredients in the product, such as garlic and black pepper, may interact with medications. Garlic may potentiate the effects of anticoagulant medications, while black pepper may affect the metabolism of certain drugs.

Dosage and Administration:

One (1) lnflamex ™ capsule daily or as directed by a licensed healthcare practitioner. Do not administer to children under the age of 12.

How Supplied:

lnflamex™ are light orange powder with black specks, in vegan hard shell capsules. One bottle contains 30 capsules (NDC 59088-191-54). Dispense in a tight, light-resistant container as defined in the USP/NF with a child resistant closure.

Storage:

Do not use if bottle seal is broken.
KEEP THIS AND ALL MEDICATIONS OUT OF THE REACH OF CHILDREN.
Store at 20° to 25°C (68° to 77°F) [see USP Controlled Room Temperature].

Inflamex™

Manufactured in the USA by:

PureTek Corporation
Panorama City, CA 91402
For questions or information
call toll-free: 877-921-7873